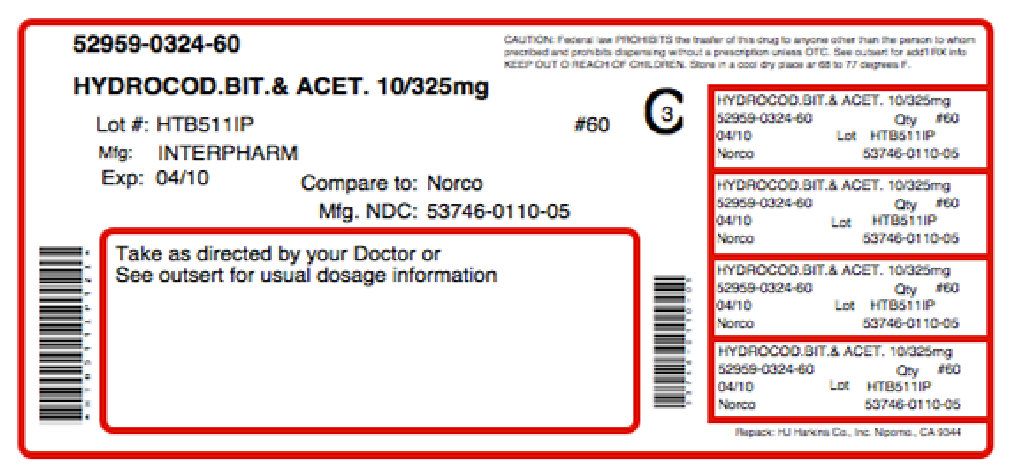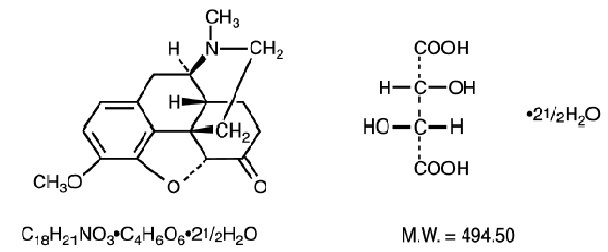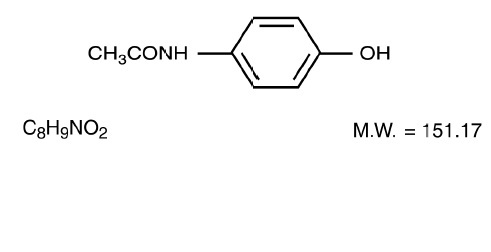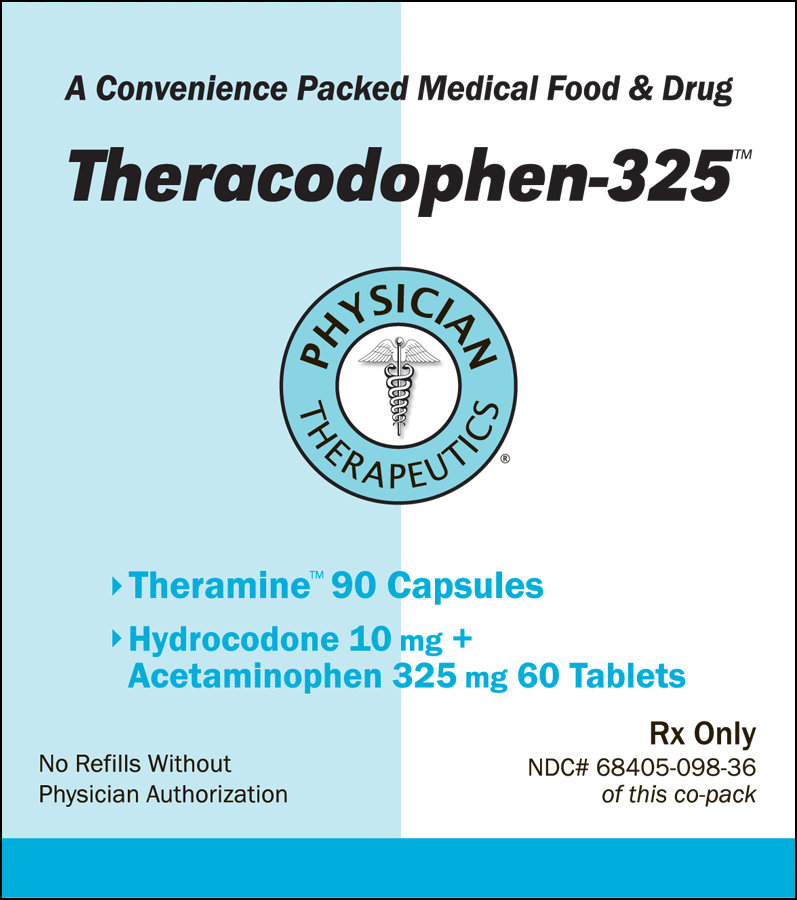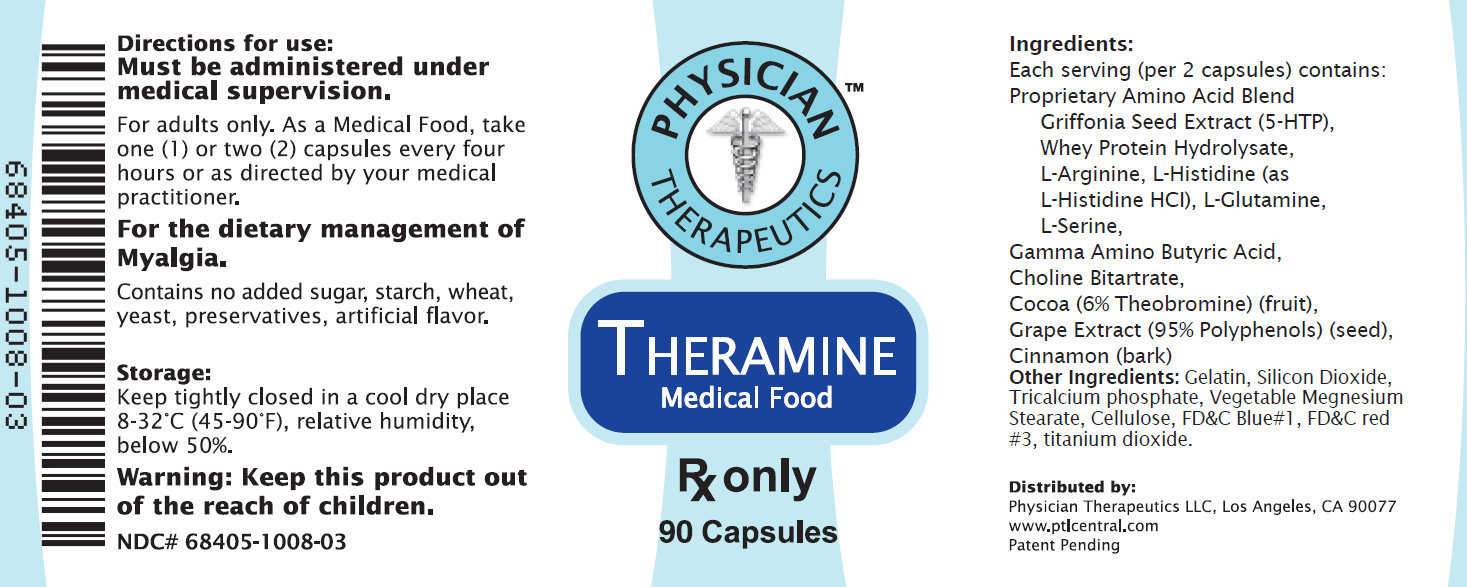 DRUG LABEL: Theracodophen-325
NDC: 68405-098 | Form: KIT | Route: ORAL
Manufacturer: Physician Therapeutics LLC
Category: prescription | Type: HUMAN PRESCRIPTION DRUG LABEL
Date: 20110801

ACTIVE INGREDIENTS: HYDROCODONE BITARTRATE 10 mg/1 1; ACETAMINOPHEN 325 mg/1 1; .GAMMA.-AMINOBUTYRIC ACID 100 mg/1 1
INACTIVE INGREDIENTS: SILICON DIOXIDE; MAGNESIUM STEARATE; CELLULOSE, MICROCRYSTALLINE; MAGNESIUM STEARATE; CELLULOSE, MICROCRYSTALLINE; MALTODEXTRIN; GELATIN

Theracodophen-325

DESCRIPTION
Hydrocodone Bitartrate and Acetaminophen Tablets, USP are supplied in tablet form for oral administration. Hydrocodone bitartrate is an opioid analgesic and antitussive and occurs as fine, white crystals or as a crystalline powder. It is affected by light. The chemical name is 4,5α-Epoxy-3-methoxy-17-methylmorphinan-6one tartrate (1:1) hydrate (2:5). It has the following structural formula:

Acetaminophen, 4' -Hydroxyacetanilide, a slightly bitter, white, odorless, crystalline powder, is a non-opiate, non-salicylate analgesic and antipyretic, It has the following structural formula:

Each Hydrocodone Bitartrate and Acetaminophen Tablets, USP contains:
Hydrocodone Bitartrate, USP. . . . . . . . . 10 mg
Acetaminophen, USP. . . . . . . . . . . . . 325 mg
In addition, each tablet contains the following inactive ingredients: colloidal silicon dioxide, crospovidone, magnesium stearate, microcrystalline cellulose, povidone, pregelatinized starch and stearic acid.
Meets USP Dissolution Test 1.

CLINICAL PHARMACOLOGY
Hydrocodone is a semisynthetic opioid analgesic and antitussive with multiple actions qualitatively similar to those of codeine. Most of these involve the central nervous system and smooth muscle. The precise mechanism of action of hydrocodone and other opiates is not known, although it is believed to relate to the existence of opiate receptors in the central nervous system. In addition to analgesia, opioids may produce drowsiness, changes in mood and mental clouding.
The analgesic action of acetaminophen involves peripheral influences, but the specific mechanism is as yet undetermined. Antipyretic activity is mediated through hypothalamic heat regulating centers. Acetaminophen inhibits prostaglandin synthetase. Therapeutic doses of acetaminophen have negligible effects on the cardiovascular or respiratory systems: however, toxic doses may cause circulatory failure and rapidm shallow breathing,

Pharmacokinetics:
The behavior of the individual components is described below.
Hydrocodone: Following a 10 mg oral dose of hydrocodone administered to five adult male subjects, the mean peak concentration was 23.6 ± 5.2 ng/mL. Maximum serum levels were achieved at 1.3 ± 0.3 hours and the half-life was determined to be 3.8 ± 0.3 hours. Hydrocodone exhibits a complex pattern of metabolism including O-demethylation, N-demethylation and 6-ketoreduction to the corresponding 6-α- and 6-β-hydroxymetabolites. See OVERDOSAGE for toxicity information.
Acetaminophen: Acetaminophen is rapidly absorbed from the gastrointestinal tract and is distributed throughout most body tissues. The plasma half-life is 1.25 to 3 hours, but may be increased by liver damage and following overdosage. Elimination of acetaminophen is principally by liver metabolism (conjugation) and subsequent renal excretion of metabolites. Approximately 85% of an oral dose appears in the urine within 24 hours of administration, most as the glucuronide conjugate, with small amounts of other conjugates and unchanged drug. See OVERDOSAGE for toxicity information.

INDICATIONS AND USAGE
Hydrocodone Bitartrate and Acetaminophen Tablets, USP are indicated for the relief of moderate to moderately severe pain.

CONTRAINDICATIONS
Hydrocodone bitartrate and acetaminophen tablets, USP should not be administered to patients who have previously exhibited hypersensitivity to hydrocodone or acetaminophen, or any other component of this product.

Patients known to be hypersensitive to other opioids may exhibit cross-sensitivity to hydrocodone.

WARNINGS
Respiratory Depression
At high doses or in sensitive patients, hydrocodone may produce dose-related respiratory depression by acting directly on the brain stem respiratory center. Hydrocodone also affects the center that controls respiratory rhythm, and may produce irregular and periodic breathing.

Head Injury and Increased Intracranial Pressure
The respiratory depressant effects of opioids and their capacity to elevate cerebrospinal fluid pressure may be markedly exaggerated in the presence of head injury, other intracranial lesions or a pre-existing increase in intracranial pressure. Furthermore, opioids produce adverse reactions which may obscure the clinical course of patients with head injuries.

Acute Abdominal Conditions
The administration of opioids may obscure the diagnosis or clinical course of patients with acute abdominal conditions.

PRECAUTIONS
General
Special Risk Patients: As with any opioid analgesic agent, hydrocodone bitartrate and acetaminophen tablets should be used with caution in elderly or debilitated patients and those with severe impairment of hepatic or renal function, hypothyroidism, Addison's disease, prostatic hypertrophy or urethral stricture. The usual precautions should be observed and the possibility of respiratory depression should be kept in mind.

Cough Reflex: Hydrocodone suppresses the cough reflex; as with all opioids, caution should be exercised when hydrocodone bitartrate and acetaminophen tablets are used postoperatively and in patients with pulmonary disease.

Information for Patients
Hydrocodone, like all opioids, may impair the mental and/or physical abilities required for the performance of potentially hazardous tasks such as driving a car or operating machinery; patients should be cautioned accordingly.

Alcohol and other CNS depressants may produce an additive CNS depression, when taken with this combination product, and should be avoided.

Hydrocodone may be habit-forming. Patients should take the drug only for as long as it is prescribed, in the amounts prescribed, and no more frequently than prescribed.

Laboratory Tests
In patients with severe hepatic or renal disease, effects of therapy should be monitored with serial liver and/or renal function tests.

Drug Interactions
Patients receiving other opioids, antihistamines, antipsychotics, anti-anxiety agents, or other CNS depressants (including alcohol) concomitantly with hydrocodone bitartrate and acetaminophen tablets may exhibit an additive CNS depression. When combined therapy is contemplated, the dose of one or both agents should be reduced.

The use of MAO inhibitors or tricyclic antidepressants with hydrocodone preparations may increase the effect of either the antidepressant or hydrocodone.

Drug/Laboratory Test Interactions
Acetaminophen may produce false-positive test results for urinary 5-hydroxyindoleacetic acid.

Carcinogenesis, Mutagenesis, Impairment of Fertility
No adequate studies have been conducted in animals to determine whether hydrocodone or acetaminophen have a potential for carcinogenesis, mutagenesis, or impairment of fertility.

Pregnancy
Teratogenic Effects: Pregnancy Category C: There are no adequate and well-controlled studies in pregnant women. Hydrocodone bitartrate and acetaminophen tablets should be used during pregnancy only if the potential benefit justifies the potential risk to the fetus.

Nonteratogenic Effects: Babies born to mothers who have been taking opioids regularly prior to delivery will be physically dependent. The withdrawal signs include irritability and excessive crying, tremors, hyperactive reflexes, increased respiratory rate, increased stools, sneezing, yawning, vomiting, and fever. The intensity of the syndrome does not always correlate with the duration of maternal opioid use or dose. There is no consensus on the best method of managing withdrawal.

Labor and Delivery
As with all opioids, administration of this product to the mother shortly before delivery may result in some degree of respiratory depression in the newborn, especially if higher doses are used.

Nursing Mothers
Acetaminophen is excreted in breast milk in small amounts, but the significance of its effects on nursing infants is not known. It is not known whether hydrocodone is excreted in human milk. Because many drugs are excreted in human milk and because of the potential for serious adverse reactions in nursing infants from hydrocodone and acetaminophen, a decision should be made whether to discontinue nursing or to discontinue the drug, taking into account the importance of the drug to the mother.

Pediatric Use
Safety and effectiveness in pediatric patients have not been established.

Geriatric Use
Clinical studies of hydrocodone bitartrate and acetaminophen did not include sufficient numbers of subjects aged 65 and over to determine whether they respond differently from younger subjects. Other reported clinical experience has not identified differences in responses between the elderly and younger patients. In general, dose selection for an elderly patient should be cautious, usually starting at the low end of the dosing range, reflecting the greater frequency of decreased hepatic, renal, or cardiac function, and of concomitant disease or other drug therapy.

Hydrocodone and the major metabolites of acetaminophen are known to be substantially excreted by the kidney. Thus the risk of toxic reactions may be greater in patients with impaired renal function due to the accumulation of the parent compound and/or metabolites in the plasma. Because elderly patients are more likely to have decreased renal function, care should be taken in dose selection, and it may be useful to monitor renal function.

Hydrocodone may cause confusion and over-sedation in the elderly; elderly patients generally should be started on low doses of hydrocodone bitartrate and acetaminophen tablets and observed closely.

ADVERSE REACTIONS
The most frequently reported adverse reactions are light-headedness, dizziness, sedation, nausea and vomiting. These effects seem to be more prominent in ambulatory than in non-ambulatory patients, and some of these adverse reactions may be alleviated if the patient lies down.

Other adverse reactions include:

Central Nervous System: Drowsiness, mental clouding, lethargy, impairment of mental and physical performance, anxiety, fear, dysphoria, psychic dependence, mood changes.

Gastrointestinal System: Prolonged administration of hydrocodone bitartrate and acetaminophen tablets may produce constipation.

Genitourinary System: Ureteral spasm, spasm of vesical sphincters and urinary retention have been reported with opiates.

Respiratory Depression: Hydrocodone bitartrate may produce dose-related respiratory depression by acting directly on the brain stem respiratory centers (see OVERDOSAGE).

Special Senses: Cases of hearing impairment or permanent loss have been reported predominantly in patients with chronic overdose.

Dermatological: Skin rash, pruritus.

The following adverse drug events may be borne in mind as potential effects of acetaminophen: allergic reactions, rash, thrombocytopenia, agranulocytosis. Potential effects of high dosage are listed in the OVERDOSAGE section.

DRUG ABUSE AND DEPENDENCE
Controlled Substance: Hydrocodone bitartrate and acetaminophen tablets are classified as a Schedule III controlled substance.

Abuse and Dependence: Psychic dependence, physical dependence, and tolerance may develop upon repeated administration of opioids; therefore, this product should be prescribed and administered with caution. However, psychic dependence is unlikely to develop when hydrocodone bitartrate and acetaminophen tablets are used for a short time for the treatment of pain.

Physical dependence, the condition in which continued administration of the drug is required to prevent the appearance of a withdrawal syndrome, assumes clinically significant proportions only after several weeks of continued opioid use, although some mild degree of physical dependence may develop after a few days of opioid therapy. Tolerance, in which increasingly large doses are required in order to produce the same degree of analgesia, is manifested initially by a shortened duration of analgesic effect, and subsequently by decreases in the intensity of analgesia. The rate of development of tolerance varies among patients.

OVERDOSAGE
Following an acute overdosage, toxicity may result from hydrocodone or acetaminophen.

Signs and Symptoms
Hydrocodone: Serious overdose with hydrocodone is characterized by respiratory depression (a decrease in respiratory rate and/or tidal volume, Cheyne-Stokes respiration, cyanosis), extreme somnolence progressing to stupor or coma, skeletal muscle flaccidity, cold and clammy skin, and sometimes bradycardia and hypotension. In severe overdosage, apnea, circulatory collapse, cardiac arrest and death may occur.

Acetaminophen: In acetaminophen overdosage: dose-dependent, potentially fatal hepatic necrosis is the most serious adverse effect. Renal tubular necrosis, hypoglycemic coma, and thrombocytopenia may also occur.

Early symptoms following a potentially hepatotoxic overdose may include: nausea, vomiting, diaphoresis and general malaise. Clinical and laboratory evidence of hepatic toxicity may not be apparent until 48 to 72 hours post-ingestion.

In adults, hepatic toxicity has rarely been reported with acute overdoses of less than 10 grams, or fatalities with less than 15 grams.

Treatment

A single or multiple overdose with hydrocodone and acetaminophen is a potentially lethal polydrug overdose, and consultation with a regional poison control center is recommended.

Immediate treatment includes support of cardiorespiratory function and measures to reduce drug absorption. Vomiting should be induced mechanically, or with syrup of ipecac, if the patient is alert (adequate pharyngeal and laryngeal reflexes). Oral activated charcoal (1 g/kg) should follow gastric emptying. The first dose should be accompanied by an appropriate cathartic. If repeated doses are used, the cathartic might be included with alternate doses as required. Hypotension is usually hypovolemic and should respond to fluids. Vasopressors and other supportive measures should be employed as indicated. A cuffed endotracheal tube should be inserted before gastric lavage of the unconscious patient and, when necessary, to provide assisted respiration.

Meticulous attention should be given to maintaining adequate pulmonary ventilation. In severe cases of intoxication, peritoneal dialysis, or preferably hemodialysis may be considered. If hypoprothrombinemia occurs due to acetaminophen overdose, vitamin K should be administered intravenously.

Naloxone, an opioid antagonist, can reverse respiratory depression and coma associated with opioid overdose. Naloxone hydrochloride 0.4 mg to 2 mg is given parenterally. Since the duration of action of hydrocodone may exceed that of the naloxone, the patient should be kept under continuous surveillance and repeated doses of the antagonist should be administered as needed to maintain adequate respiration. An opioid antagonist should not be administered in the absence of clinically significant respiratory or cardiovascular depression.

If the dose of acetaminophen may have exceeded 140 mg/kg, acetylcysteine should be administered as early as possible. Serum acetaminophen levels should be obtained, since levels four or more hours following ingestion help predict acetaminophen toxicity. Do not await acetaminophen assay results before initiating treatment. Hepatic enzymes should be obtained initially, and repeated at 24-hour intervals.

Methemoglobinemia over 30% should be treated with methylene blue by slow intravenous administration.

The toxic dose for adults for acetaminophen is 10 g.

DOSAGE AND ADMINISTRATION
Dosage should be adjusted according to the severity of the pain and the response of the patient. However, it should be kept in mind that tolerance to hydrocodone can develop with continued use and that the incidence of untoward effects is dose related.

The usual adult dosage is one or two tablets every four to six hours as needed for pain. The total daily dose should not exceed 6 tablets.

HOW SUPPLIED
Hydrocodone Bitartrate and Acetaminophen Tablets, USP, 10 mg / 325 mg are available as white to off white, scored, oblong biconvex tablets, debossed “IP 110” on obverse and bisected on the reverse. Each tablet contains 10 mg hydrocodone bitartrate and 325 mg acetaminophen.

They are supplied as follows:

Bottles of 100: NDC 53746-110-01

Bottles of 500: NDC 53746-110-05

Bottles of 1000: NDC 53746-110-10

Storage: Store at 25°C (77°F); excursions permitted to 15° to 30°C (59° to 86°F). [see USP Controlled Room Temperature].

Dispense in a tight, light-resistant container with a child-resistant closure.

Manufactured by:

Amneal Pharmaceuticals of NY

Hauppauge, NY 11788

Distributed by:

Amneal Pharmaceuticals

Glasgow, KY 42141

Rev. 12-2009

PACKAGE LABEL

Packaged by Bryant Ranch North Hollywood CA 91605

Hydrocodone/Apad 10/325 mg (CIII)

Compare To

Norco 10/325 mg (CIII) Tablet

Wilming xx xxx Inc Pharmaceutical Group

#60 EXP 11/09
NDC 6362929476

NANA

LOT 10040 Rx

May Cause Drowsiness/No Alcohol

Take with food

Theramine™ PRODUCT INFORMATION
Theramine (U.S. patent pending) capsules by oral administration. A specially formulated Medical Food product, consisting of a proprietary blend of amino acids and polyphenol ingredients in specific proportions, for the dietary management of the metabolic processes associated with pain disorders and inflammatory conditions. (PD) (IC). Must be administered under physician supervision.
Medical Foods
Medical Food products are often used in hospitals (e.g., for burn victims or kidney dialysis patients) and outside of a hospital setting under a physician’s care for the dietary management of diseases in patients with particular medical or metabolic needs due to their disease or condition. Congress defined "Medical Food" in the Orphan Drug Act and Amendments of 1988 as "a food which is formulated to be consumed or administered enterally [or orally] under the supervision of a physician and which is intended for the specific dietary management of a disease or condition for which distinctive nutritional requirements, based on recognized scientific principles, are established by medical evaluation." Medical Foods are complex formulated products, requiring sophisticated and exacting technology. Theramine has been developed, manufactured, and labeled in accordance with both the statutory and the FDA regulatory definition of a Medical Food. Theramine must be used while the patient is under the ongoing care of a physician.
PAIN DISORDERS (PD) INFLAMMATORY CONDITIONS (IC)
PD and IC as a Metabolic Deficiency Disease
A critical component of the definition of a Medical Food is the requirement for a distinctive nutritional deficiency. FDA scientists have proposed a physiologic definition of a distinctive nutritional deficiency as follows: “the dietary management of patients with specific diseases requires, in some instances, the ability to meet nutritional requirements that differ substantially from the needs of healthy persons. For example, in establishing the recommended dietary allowances for general, healthy population, the Food and Nutrition Board of the Institute of Medicine National Academy of Sciences, recognized that different or distinctive physiologic requirements may exist for certain persons with "special nutritional needs arising from metabolic disorders, chronic diseases, injuries, premature birth, other medical conditions and drug therapies. Thus, the distinctive nutritional needs associated with a disease reflects the total amount needed by a healthy person to support life or maintain homeostasis, adjusted for the distinctive changes in the nutritional needs of the patient as a result of the effects of the disease process on absorption, metabolism and excretion.” It was also proposed that in patients with certain disease states who respond to nutritional therapies, a physiologic deficiency of the nutrient is assumed to exist. For example, if a patient with pain disorders responds to a tryptophan formulation by decreasing perceived pain, a deficiency of tryptophan is assumed to exist. Patients with pain disorders and inflammatory conditions are known to have nutritional deficiencies of tryptophan, choline, arginine, GABA, flavonoids, and certain antioxidants. Patients with pain disorders and inflammatory conditions frequently exhibit reduced plasma levels of tryptophan and GABA and have been shown to respond to oral administration of GABA, arginine, tryptophan, or a 5-hydoxytryptophan formulation. Research has shown that tryptophan, arginine or GABA reduced diets result in a fall of circulating tryptophan, arginine, and/or GABA.
Patients with pain disorders frequently exhibit activation of the degradation pathways that increases the turnover of GABA, arginine and/or tryptophan leading to a reduced level of production of serotonin, GABA or nitric oxide for a given precursor blood level. Research has also shown that a genetic predisposition to accelerated degradation can lead to increased precursor requirements in certain patients with pain disorders and inflammatory conditions.
Choline is required to fully potentiate acetylcholine synthesis by brain neurons. A deficiency of choline leads to reduced acetylcholine production by the neurons. Flavonoids potentiate the production of acetylcholine by the neurons thereby reducing delta pain. Diets deficient in flavonoid rich foods and choline result in inadequate flavonoid concentrations, impeding acetylcholine production in certain patients with pain disorders and/or inflammatory conditions. Acetylcholine in pre-synaptic ganglia is necessary for the production of serotonin and nitric oxide in post-synaptic ganglia. Provision of tryptophan, arginine, GABA, choline and flavonoids with antioxidants, in specific proportions can restore the production of beneficial serotonin, nitric oxide, and acetylcholine, thereby reducing the perception of pain and reducing inflammation. L-Histidine is known to produce brain histamine that stimulates production of ACTH.

PRODUCT DESCRIPTION
Primary Ingredients Theramine consists of a proprietary blend of amino acids, cocoa, caffeine, cinnamon, and flavonoids in specific proportions. These ingredients fall into the category of Generally Regarded as Safe” (GRAS) as defined by the Food and Drug Administration (FDA) (Sections 201(s) and 409 of the Federal Food, Drug, and Cosmetic Act). A GRAS substance is distinguished from a food additive on the basis of the common knowledge about the safety of the substance for its intended use. The standard for an ingredient to achieve GRAS status requires not only technical demonstration of non-toxicity and safety, but also general recognition of safety through widespread usage and agreement of that safety by experts in the field. Many ingredients have been determined by the U.S. Food and Drug Administration (FDA) to be GRAS, and are listed as such by regulation, in Volume 21 Code of Federal Regulations (CFR) Sections 182, 184, and 186.
Amino Acids
Amino Acids are the building blocks of protein. All amino acids are GRAS listed as they have been ingested by humans for thousands of years. The doses of the amino acids in Theramine are equivalent to those found in the usual human diet. Patients with pain disorders may require an increased amount of certain amino acids that cannot be obtained from normal diet alone. Tryptophan, for example, is an obligatory amino acid. The body cannot make tryptophan and must obtain tryptophan from the diet. Tryptophan is needed to produce serotonin. Serotonin is required to reduce pain. Patients with pain disorders and inflammatory conditions have altered serotonin metabolism. Some patients with pain disorders and inflammatory conditions have a resistance to the use of tryptophan that is similar to the mechanism found in insulin resistance. Patients with pain disorders and inflammatory conditions cannot acquire sufficient tryptophan from the diet to alter the perception of pain and the inflammatory process without ingesting a prohibitively large amount of calories, particularly calories from protein.
Flavonoids
Flavonoids are a group of phytochemical compounds found in all vascular plants including fruits and vegetables. They are a part of a larger class of compounds known as polyphenols. Many of the therapeutic or health benefits of colored fruits and vegetables, cocoa, red wine, and green tea are directly related to their flavonoid content. The specially formulated flavonoids found in Theramine cannot be obtained from conventional foods in the necessary proportions to elicit a therapeutic response.
Other Ingredients
Theramine contains the following inactive or other ingredients, as fillers, excipients, and colorings: magnesium stearate, microcrystalline cellulose, Maltodextrin NF, gelatin (as the capsule material).
Physical Description
Theramine is a yellow to light brown powder. Theramine contains L-Glutamine, L-Arginine, L-Histidine, and L-Serine, 5-Hydroxytryptophan as Griffonia Seed Extract, GABA, Choline Bitartrate, Cinnamon, Cocoa, Hydrolyzed Whey Protein, and Grape Seed Extract.

CLINICAL PHARMACOLOGY
Mechanism of Action
Theramine acts by restoring and maintaining the balance of the neurotransmitters; GABA, nitric oxide, serotonin, and acetylcholine that are associated with pain disorders and inflammatory conditions. Theramine stimulates the production ACTH to reduce inflammation.
Metabolism
The amino acids in Theramine are primarily absorbed by the stomach and small intestines. All cells metabolize the amino acids in Theramine. Circulating tryptophan, arginine and choline blood levels determine the production of serotonin, nitric oxide, and acetylcholine.
Excretion
Theramine is not an inhibitor of cytochrome P450 1A2, 2C9, 2C19, 2D6, or 3A4. These isoenzymes are principally responsible for 95% of all detoxification of drugs, with CYP3A4 being responsible for detoxification of roughly 50% of drugs. Amino acids do not appear to have an effect on drug metabolizing enzymes.

INDICATIONS FOR USE
Theramine is intended for the clinical dietary management of the metabolic processes of pain disorders and inflammatory conditions.

CLINICAL EXPERIENCE
Administration of Theramine has demonstrated significant reduction in symptoms of pain and inflammation in patients with acute and chronic pain when used for the dietary management of the metabolic processes associated with pain disorders and inflammatory conditions. Administration of Theramine results in the induction and maintenance of pain relief in patients with pain disorders and inflammatory conditions.

PRECAUTIONS AND CONTRAINDICATIONS
Theramine is contraindicated in an extremely small number of patients with hypersensitivity to any of the nutritional components of Theramine.

ADVERSE REACTIONS
Oral supplementation with L-tryptophan, L-arginine or choline at high doses up to 15 grams daily is generally well tolerated. The most common adverse reactions of higher doses — from 15 to 30 grams daily — are nausea, abdominal cramps, and diarrhea. Some patients may experience these symptoms at lower doses. The total combined amount of amino acids in each Theramine capsule does not exceed 400 mg.

DRUG INTERACTIONS
Theramine does not directly influence the pharmacokinetics of prescription drugs. Clinical experience has shown that administration of Theramine may allow for lowering the dose of co-administered drugs under physician supervision.

OVERDOSAGE

OVERDOSE
There is a negligible risk of overdose with Theramine as the total dosage of amino acids in a one month supply (90 capsules) is less than 36 grams. Overdose symptoms may include diarrhea, weakness, and nausea.
POST-MARKETING SURVEILLANCE
Post-marketing surveillance has shown no serious adverse reactions. Reported cases of mild rash and itching may have been associated with allergies to Theramine flavonoid ingredients, including cinnamon, cocoa, and chocolate. These reactions were transient in nature and subsided within 24 hours.

DOSAGE AND ADMINISTRATION
Recommended Administration For the dietary management of the metabolic processes associated with pain disorders and inflammatory conditions. Take (2) capsules one to three times daily or as directed by physician. As with most amino acid formulations Theramine should be taken without food to increase the absorption of key ingredients.

How Supplied
Theramine is supplied in purple and white, size 0 capsules in bottles of 60 or 90 capsules.
Physician Supervision
Theramine is a Medical Food product available by prescription only and must be used while the patient is under ongoing physician supervision.
U.S. patent pending.
Manufactured by Arizona Nutritional Supplements, Inc. Chandler AZ 85225
Distributed by Physician Therapeutics LLC, Los Angeles, CA 90077. www.ptlcentral.com
Copyright 2003-2006, Physician Therapeutics LLC, all rights reserved
NDC: 68405-1008-02
NDC: 68405-1008-03

Storage
Store at room temperature, 59-86OF (15-30OC) Protect from light and moisture. Theramine is supplied to physicians in a recyclable plastic bottle with a child-resistant cap.

PACKAGE LABEL

PHYSICIAN THERAPEUTICS THERAMINE Medical Food Rx only 90 Capsules Directions for use: Must be administered under medical supervision. For adults only. As a Medical Food, take one (1) or two (2) capsules every four hours or as directed by your medical practitioner. For the dietary management of Myalgia. Contains no added sugar, starch, wheat, yeast, preservatives, artificial flavor. Storage: Keep tightly closed in a cool dry place 8-32^0 C (45-90^0 F), relative humidity, below 50%. Warning: Keep this product out of the reach of children. NDC# 68405-1008-03 Ingredients: Each serving (per 2 capsules) contains: Proprietary Amino Acid Blend Griffonia Seed Extract (5-HTP), Whey Protein Hydrolysate, L-Arginini, L-Histidine (as L-Histidine HCl), L-Glutamine, L-Serine, Gamma Amino Butyric Acid, Choline Bitartrate, Cocoa (6% Theobromine) (fruit), Grape Extract (95% Polyphenols) (seed), Cinnamon (bark) Other Ingredients: Gelatin, Silicon Dioxide, Tricalcium phosphate, Vegetable Magnesium Stearate, Cellulose, FD and C Blue #1, FD and C red#3, titanium dioxide. Distributed by: Physician Therapeutics LLC, Los Angeles, CA 90077 www.ptlcentral.com Patent Pending

PACKAGE LABEL

A Convenience Packed Medical Food and Drug
Theracodophen-325
PHYSICIAN THERAPEUTICS
Theramine 90 Capsules
Hydrocodone 10mg + Acetaminophen 325mg 60 Tablets
No Refills Without Physician Authorization
Rx Only
NDC# 68405-8098-36 of this co-pack
For the Dietary Management of Pain and Inflammation.
Two capsules twice daily or as directed by physician. See product label and insert
Theramine
Medical Food
As prescribed by physician. See product label and product information insert.
Hydrocodone 10mg + Acetaminophen 325mg
Rx Drug